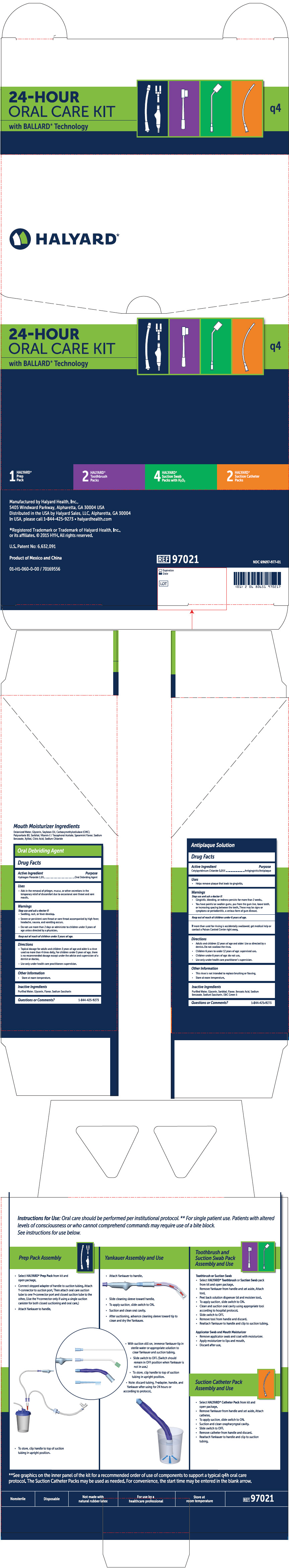 DRUG LABEL: Oral Care Q4 Kit
NDC: 69697-986 | Form: KIT | Route: ORAL
Manufacturer: Halyard Health
Category: otc | Type: HUMAN OTC DRUG LABEL
Date: 20160126

ACTIVE INGREDIENTS: Hydrogen peroxide 0.015 mg/1 mL; Cetylpyridinium  Chloride 0.0005 mg/1 mL
INACTIVE INGREDIENTS: Water; Glycerin; Mint; Saccharin Sodium Dihydrate; Water; Benzoic Acid; Saccharin Sodium Dihydrate; Sodium Benzoate; Glycerin; D&C Green No. 5; Sorbitol; Mint

Halyard
24-Hour Oral Care Kit

Oral Debriding Agent

Drug Facts

Active Ingredient

Hydrogen Peroxide 1.5%

Purpose

Oral Debriding Agent

Uses

- Aids in the removal of phlegm, mucus, or other secretions in the temporary relief of discomfort due to occasional sore throat and sore mouth.

Warnings

Stop use and ask a doctor if:

- Swelling, rash, or fever develop.
- Severe or persistent sore throat or sore throat accompanied by high fever, headache, nausea, and vomiting occurs.

- Do not use more than 2 days or administer to children under 3 years of age unless directed by a physician.

Keep out of reach of children under 3 years of age.

Directions

- Topical dosage for adults and children 3 years of age and older is a rinse used no more than 4 times daily. For children under 3 years of age, there is no recommended dosage except under the advice and supervision of a dentist or doctor.
- Use only under health care practitioners supervision.

Other Information

- Store at room temperature.

Inactive Ingredients

Purified Water, Glycerin, Flavor, Sodium Saccharin

Questions or Comments?

1-800-KCHELPS

Antiplaque Solution

Drug Facts

Active Ingredient

Cetylpyridinium Chloride 0.05%

Purpose

Antigingivitis/Antiplaque

Uses

- Helps remove plaque that leads to gingivitis.

Warnings

Stop use and ask a doctor if:

- Gingivitis, bleeding, or redness persists for more than 2 weeks.
- You have painful or swollen gums, pus from the gum line, loose teeth, or increasing spacing between the teeth. These may be signs or symptoms or periodontitis, a serious form of gum disease.

Keep out of reach of children under 6 years of age.

If more than used for rinsing is accidently swallowed, get medical help or contact a Poison Control Center right away.

Directions

- Adults and children 12 years of age and older: Use as directed by a dentist. DO not swallow the rinse.
- Children 6 years to under 12 years of age: supervised use.
- Children under 6 years of age: do not use.
- Use only under health care practitioner's supervision.

Other Information

- This rinse is not intended to replace brushing or flossing.
- Store at room temperature.

Inactive Ingredients

Purified Water, Glycerin, Sorbitol, Flavor, Benzoic Acid, Sodium Benzoate, Sodium Saccharin, D&C Green 5

Questions or Comments?

1-844-425-9273

Manufactured by Kimberly-Clark, Roswell, GA 30076 USA

Distributed in the U.S. by Kimberly-Clark Global Sales, LLC, Roswell, GA 30076 USA

PRINCIPAL DISPLAY PANEL - Kit Carton

HALYARD*

24-HOUR
ORAL CARE KIT
with BALLARD* Technology

q4

1
HALYARD*
Prep
Pack

2
HALYARD*
Toothbrush
Packs

4
HALYARD*
Suction Swab
Packs with H2O2

2
HALYARD*
Suction Catheter
Packs